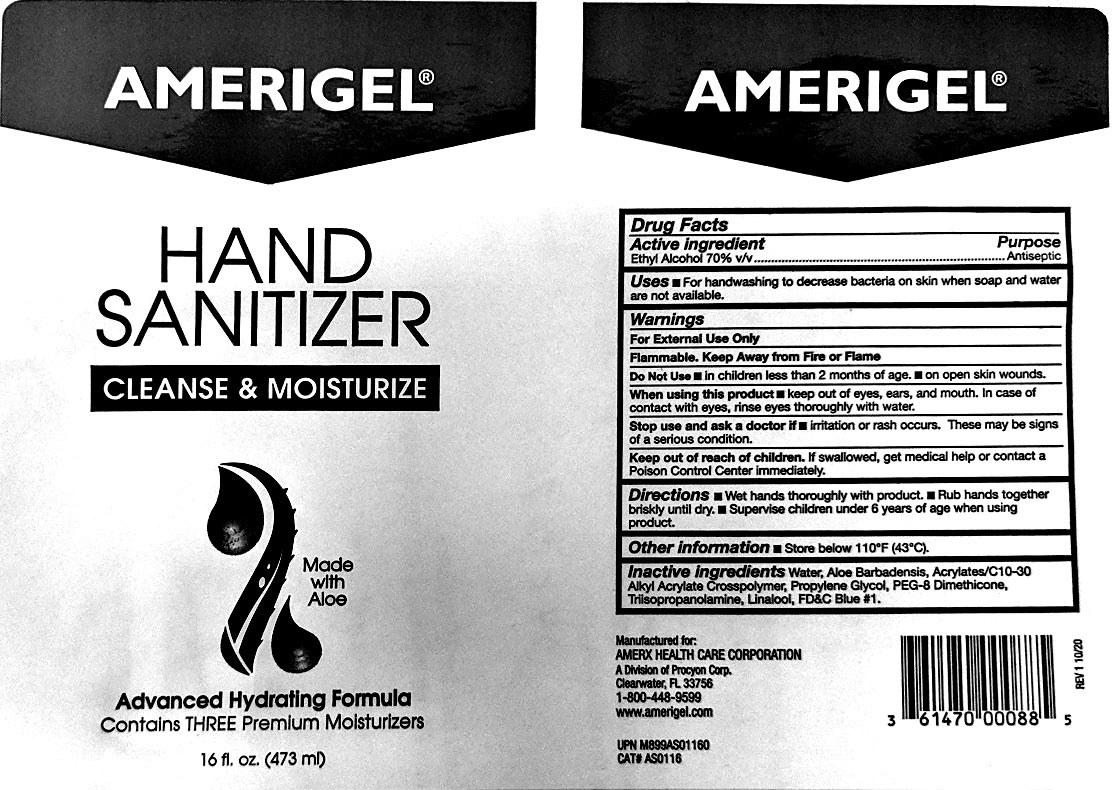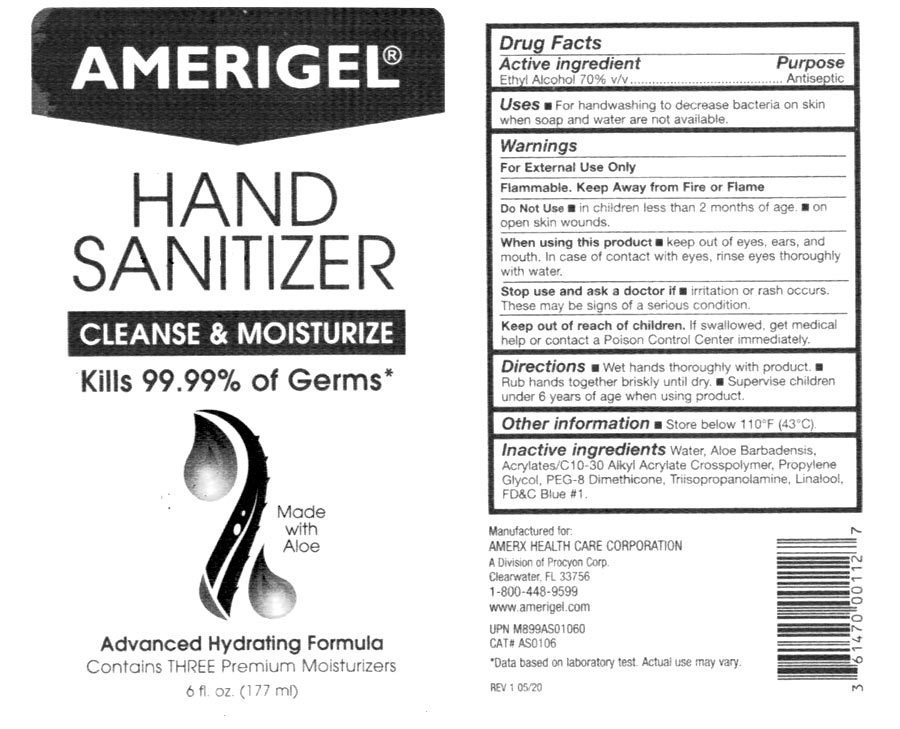 DRUG LABEL: Amerigel Hand Sanitizer
NDC: 79417-010 | Form: GEL
Manufacturer: Kova Laboratories, Inc.
Category: otc | Type: HUMAN OTC DRUG LABEL
Date: 20201201

ACTIVE INGREDIENTS: ALCOHOL 70 L/100 L
INACTIVE INGREDIENTS: WATER 28.397 L/100 L; ALOE VERA LEAF 0.05 L/100 L; LINALOOL, (+/-)- 0.07 L/100 L; CARBOMER 1342 0.27 L/100 L; PROPYLENE GLYCOL 0.5 L/100 L; PEG-8 DIMETHICONE 0.3 L/100 L; TRIISOPROPANOLAMINE 0.41 L/100 L; FD&C BLUE NO. 1 0.003 L/100 L

Active Ingredient(s)

Alcohol 70% v/v. Purpose: Antiseptic

Purpose

Antiseptic, Hand Sanitizer

Use

Hand Sanitizer to help reduce bacteria that potentially can cause disease. For use when soap and water are not available.

Warnings

For external use only. Flammable. Keep away from heat or flame

Do not use

- in children less than 2 months of age
- on open skin wounds

When using this product keep out of eyes, ears, and mouth. In case of contact with eyes, rinse eyes thoroughly with water.
Stop use and ask a doctor if irritation or rash occurs. These may be signs of a serious condition.
Keep out of reach of children. If swallowed, get medical help or contact a Poison Control Center right away.

Stop use and ask a doctor if irritation or rash occurs. These may be signs of a serious condition.

Keep out of reach of children. If swallowed, get medical help or contact a Poison Control Center right away.

Directions

- Place enough product on hands to cover all surfaces. Rub hands together until dry.
- Supervise children under 6 years of age when using this product to avoid swallowing.

Other information

- Store below 110F (43C)

Inactive ingredients

Purified water USP, Aloe Barbadensis, acrylates/C10-30 alkyl acrylate crosspolymer, Propylene Glycol, PEG-8 Dimethicone, Triisopropanolamine, Linalool, FD&C #1